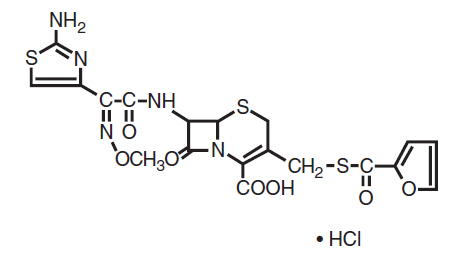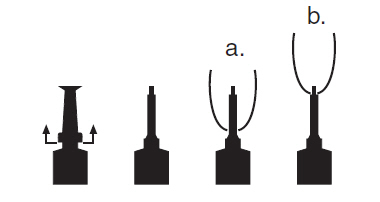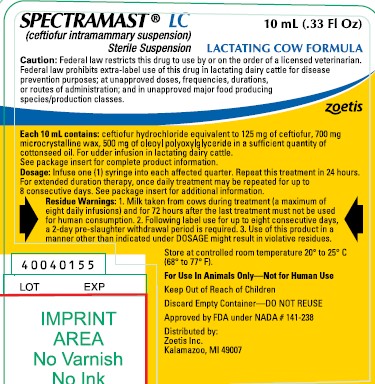 DRUG LABEL: Spectramast
NDC: 54771-5279 | Form: SUSPENSION
Manufacturer: Zoetis Inc.
Category: animal | Type: PRESCRIPTION ANIMAL DRUG LABEL
Date: 20250326

ACTIVE INGREDIENTS: CEFTIOFUR HYDROCHLORIDE 125 mg/10 mL
INACTIVE INGREDIENTS: MICROCRYSTALLINE WAX 700 mg/10 mL; APRICOT KERNEL OIL PEG-6 ESTERS

SPECTRAMAST® LC

SPECTRAMAST® LC

(ceftiofur intramammary suspension)

Sterile Suspension

For Intramammary Infusion in Lactating Cows Only

FOR USE IN ANIMALS ONLY — NOT FOR HUMAN USE

CAUTION

Federal law restricts this drug to use by or on the order of a licensed veterinarian. Federal law prohibits extra-label use of this drug in lactating dairy cattle for disease prevention purposes; at unapproved doses, frequencies, durations, or routes of administration; and in unapproved major food producing species/production classes.

DESCRIPTION

Ceftiofur hydrochloride is a cephalosporin antibiotic.

Chemical Structure of Ceftiofur Hydrochloride

U-64279A

Chemical Name of Ceftiofur Hydrochloride

5-Thia-1-azabicyclo [4.2.0] oct-2-ene-2-carboxylic acid, 7 -[[2-(2-

amino-4-thiazolyl) - 2 -(methoxyimino)acetyl]amino]-3-[[(2-furanylcarbonyl)

thio]methyl]-8-oxo, hydrochloride.

SPECTRAMASTR LC Sterile Suspension is an oil based sterile

suspension.

Each 10 mL PLASTETR Disposable Syringe Contains:

Ceftiofur Equivalents (as the hydrochloride salt) ....................125 mg

Microcrystalline Wax ..............................................................700 mg

Oleoyl Polyoxylglyceride ........................................................500 mg

Cottonseed Oil .............................................................................q.s.

INDICATIONS FOR USE

SPECTRAMAST® LC (ceftiofur intramammary suspension) Sterile Suspension is indicated for use in lactating dairy cattle for (1) the treatment of clinical mastitis associated with coagulase-negative staphylococci, Streptococcus dysgalactiae, and Escherichia coli and (2) the treatment of diagnosed subclinical mastitis associated with coagulase-negative staphylococci and Streptococcus dysgalactiae.

DOSAGE

Infuse one (1) syringe into each affected quarter. Repeat this treatment in 24 hours. For extended duration therapy, once daily treatment may be repeated for up to 8 consecutive days.

DIRECTIONS FOR USING THE PLASTET® DISPOSABLE SYRINGE

The syringe is designed to provide the choice of either insertion of the full cannula as has traditionally been practiced, or insertion of no more than 1/8 inch of the cannula, as reported by Eberhart, R.J., et. al. 1987. Current Concepts of Bovine Mastitis, 3rd Edition, National Mastitis Council, Arlington, VA.

a. Full insertion: Remove the red end cap by pulling straight up as shown. Gently insert the full cannula into the teat canal; carefully infuse the product.

b. Partial insertion: Remove the red end cap by pulling straight up as shown. Gently insert the exposed white tip into the teat canal; carefully infuse the product.

Syringe image

ADMINISTRATION

Treatment: Wash teats thoroughly with warm water containing a suitable dairy antiseptic. Dry teats thoroughly. Milk out udder completely. Using an appropriate antiseptic teat wipe (containing at least 70% isopropyl alcohol), wipe off the end of the affected teat using a separate wipe for each teat. Choose the desired insertion length (full or partial) and insert tip into teat canal; push plunger to dispense entire contents, massage the quarter to distribute the suspension into the milk cistern.

CONTRAINDICATIONS

As with all drugs, the use of SPECTRAMAST® LC Sterile Suspension is contraindicated in animals previously found to be hypersensitive to the drug.

Discard Empty Container: DO NOT REUSE

KEEP OUT OF REACH OF CHILDREN

WARNINGS

Penicillins and cephalosporins can cause allergic reactions in sensitized individuals. Topical exposures to such antimicrobials, including ceftiofur, may elicit mild to severe allergic reactions in some individuals. Repeated or prolonged exposure may lead to sensitization. Avoid direct contact of the product with the skin, eyes, mouth and clothing. Sensitization of the skin may be avoided by wearing protective gloves.

Persons with a known hypersensitivity to penicillin or cephalosporins should avoid exposure to this product.

In case of accidental eye exposure, flush with water for 15 minutes. In case of accidental skin exposure, wash with soap and water. Remove contaminated clothing. If allergic reaction occurs (e.g., skin rash, hives, difficult breathing), seek medical attention.

The Safety Data Sheet contains more detailed occupational safety information. For a copy of the Safety Data Sheet or to report adverse reactions, call Zoetis Inc. at 1-888-963-8471. For additional information about adverse drug experience reporting for animal drugs, contact FDA at 1-888-FDA-VETS or at www.fda.gov/reportanimalae.

CONTACT INFORMATION

The Safety Data Sheet contains more detailed occupational safety information. For a copy of the Safety Data Sheet or to report adverse reactions, call Zoetis Inc. at 1-888-963-8471. For additional information about adverse drug experience reporting for animal drugs, contact FDA at 1-888-FDA-VETS or at www.fda.gov/reportanimalae.

RESIDUE WARNINGS

1. Milk taken from cows during treatment (a maximum of eight daily infusions) and for 72 hours after the last treatment must not be used for human consumption.

2. Following label use for up to eight consecutive days, a 2-day pre-slaughter withdrawal period is required.

3. Use of this product in a manner other than indicated under DOSAGE might result in violative residues.

PRECAUTION

Following intramammary infusion with antibiotics in lactating cows, milk obtained during treatment and during the milk discard period should be properly discarded and not fed to calves. SPECTRAMAST LC is intended for use in lactating dairy cattle with mastitis associated only with the specified labeled pathogens. To assure responsible antimicrobial drug use, it is expected that subclinical mastitis will be diagnosed using a positive culture or other pathogen-specific test in addition to any other appropriate veterinary medical evaluation prior to treatment. Cows with systemic clinical signs caused by mastitis should receive other appropriate therapy under the direction of a licensed veterinarian. After successful treatment, reinfection may occur unless good herd management, sanitation, and mechanical safety measures are practiced. Affected cows should be watched carefully to detect recurrence of infection and possible spread to other animals.

CLINICAL MICROBIOLOGY

Ceftiofur is a broad-spectrum cephalosporin antibiotic that exerts its effect by inhibiting bacterial cell wall synthesis. Like other s-lactam antimicrobial agents, cephalosporins inhibit cell wall synthesis by interfering with the enzymes essential for peptidoglycan synthesis. This effect results in lysis of the bacterial cell and accounts for the bactericidal nature of these agents. Ceftiofur has demonstrated in vitro activity against coagulase-negative staphylococci, Streptococcus dysgalactiae, and Escherichia coli. The minimum inhibitory concentrations (MICs) of ceftiofur against indicated pathogens collected from field studies conducted in 2000 were determined using methods recommended by the National Committee for Clinical Laboratory Standards (NCCLS, M31-A) and are represented in Table 1, below:

Table 1. Ceftiofur Minimum Inhibitory Concentrations (MIC)
Values* of Isolates from Field Studies Evaluating Clinical Mastitis in Dairy Cows in the U.S. during 2000

Pathogen | Number of Isolates | MIC90**; (μg/mL) | MIC Range; (μg/mL)
Coagulase-negative 33 1.0 ≤0.06–2.0; staphylococci (CNS) | 33 | 1.0 | ≤0.06–2.0
Streptococcus dysgalactiae | 32 | ≤0.06 | ≤0.06–0.5
Escherichia coli | 35 | 0.5 | ≤0.06–1.0

* The correlation between in vitro susceptibility data and clinical effectiveness is unknown.

** The lowest MIC to encompass 90% of the most susceptible isolates.

EFFECTIVENESS

In 1999 to 2000, the efficacy of ceftiofur was demonstrated in a pivotal multi-location field trial in lactating dairy cattle with clinical mastitis in one quarter. Ceftiofur was formulated in stable cottonseed oil sterile suspension manufactured under GMP guidelines. Cows with mastitis were enrolled in the study if visually abnormal milk (clots, flakes, or watery secretion) or if udder swelling, heat, pain or redness were present and the milk was not yet visually abnormal but California Mastitis Test (CMT) gave results of 2 or greater. A total of 13 trial sites enrolled 352 cows in the study. Cows were assigned to one of three treatment groups: non-treated control, 62.5 mg ceftiofur, and 125 mg ceftiofur. Each treatment group received an intramammary infusion twice at a 24-hour interval in the affected quarter. The non-treated controls received no therapy. Three different definitions for cure were used for analysis purposes: 1) a clinical cure was defined as the milk and udder returning to normal 14 days after the last treatment and remaining normal at the 21 day time point; 2) a bacterial cure was defined as the absence of the pre-treatment pathogen at 14 and 21 days post-treatment; 3) a protocol cure was defined as the absence of the pre-treatment pathogen at 14 and 21 days post-treatment and return to normal of the milk and udder 14 days after the last treatment and remaining normal at the 21 day time point. Three hundred and thirty seven cows were analyzed for clinical cure rates, which were 54.7% (64/117) for the non-treated control group compared to 69.4% (75/108) for the 62.5 mg treatment group and 78.6% (88/112) for the 125 mg treatment group. The 125 mg treatment group’s clinical cure rate was significantly greater than the non-treated control (P=0.002). One hundred and forty six cows were analyzed for bacterial cure rates, which were 41.3% (19/46) for the non-treated control group, 45.6% (21/46) for the 62.5 mg treatment group and 70.4% (38/54) for the 125 mg treatment group. The 125 mg treatment group’s bacterial cure rate was significantly greater than the non-treated control group (P=0.006). One hundred and forty six cows were analyzed for protocol cure rates, which were 63.0% (34/54) for the 125 mg treatment group, 41.3% (19/46) for the 62.5 mg treatment group and 23.9% (11/46) for the non-treated control group. The 125 mg treatment group’s protocol cure rate was significantly better than the non-treated control (P<0.001) for treatment of clinical mastitis. Thus, 125 mg of ceftiofur administered via intramammary infusion twice at a 24-hour interval was effective in the treatment of clinical mastitis in lactating dairy cows associated with coagulase-negative staphylococci, (CNS), Streptococcus dysgalactiae, and Escherichia coli.

The effectiveness of ceftiofur for the treatment of subclinical mastitis was demonstrated in a 10-site field study in lactating dairy cattle in 2013. Cows with subclinical mastitis were enrolled in the study if milk and udders were visually normal, composite quantitative somatic cell count (SCC) was >400,000 cells/mL, and milk culture was positive for a mastitis-causing pathogen. Cows were assigned to one of two treatment groups: SPECTRAMAST LC (125 mg ceftiofur equivalents per dose) or an equivalent volume of saline. Each treatment group received an intramammary infusion twice at a 24-hour interval in the affected quarter. Treatment success (bacterial cure) was defined as the absence of the pre-treatment pathogen at 14 and 20 days post-treatment. Three hundred thirty-six cows were analyzed for bacterial cure rates. There was a statistically significantly different (P < 0.0001) overall proportion of treatment successes in the SPECTRAMAST LC-treated group (44%, 75/164) compared with the saline-treated group (4%, 8/172). Additionally, a clinically-relevant ratio of clinical successes to failures was observed in the SPECTRAMAST LC-treated group compared to the saline-treated group for evaluable cases of subclinical mastitis associated with CNS and with S. dysgalactiae.

ANIMAL SAFETY

A pivotal GLP udder irritation study was conducted in 40 cows to assess udder irritation following daily intramammary infusion of an oil‑based suspension containing 125 mg of ceftiofur for up to 8 consecutive days. A transient and clinically insignificant rise in SCC to levels <200,000 cell/mL was observed following infusion in normal cows with very low pre-infusion SCC (<10,000 cell/mL). This elevation is not unexpected with oil-based suspensions. The duration of therapy did not affect this elevation. No udder clinical signs of irritation (swelling, pain, or redness), changes in body temperature or in milk production were noted during this study. This pivotal GLP study demonstrated that this formulation is clinically safe and non-irritating to the udder of lactating dairy cows. In two clinical field efficacy studies in 971 lactating dairy cows, no reports of udder irritation or adverse events were noted following infusion. Collectively, these three studies demonstrate that the intramammary infusion of an oil-based suspension containing 125 mg of ceftiofur once daily into all four quarters for up to 8 consecutive days is clinically safe and nonirritating to the udder of lactating dairy cows.

MILK AND TISSUE RESIDUE DEPLETION

A metabolism study in cattle using radiolabeled ceftiofur provided the data to establish tolerances for ceftiofur-related residues (as desfuroylceftiofur) in tissue and milk. These tolerances are 0.1 ppm in milk, 0.4 ppm in kidney, 2.0 ppm in liver, and 1.0 ppm in muscle.

Two pivotal milk residue decline studies were conducted. In these studies, non-mastitic cows received 125 mg of ceftiofur per quarter into all four quarters either twice at a 24-hour interval or once daily for 8 consecutive days. Regardless of treatment duration and using a tolerance of 0.10 ppm for ceftiofur-related residues in milk, these studies demonstrate that milk taken during treatment (a maximum of 8 consecutive daily infusions) and for 72 hours after the last treatment must not be used for human consumption and must be discarded.

A pivotal tissue residue decline study in lactating dairy cattle provides tissue residue decline data. In this study, the cattle received an intramammary infusion of 125 mg of ceftiofur hydrochloride into each of four quarters once daily for 8 consecutive days. Ceftiofur residues were determined in the kidney (the target tissue) using the official analytical method. Kidney residues were less than the established tolerance (0.4 ppm) by 2 days after the last infusion. These data collectively support the assignment of a 2-day pre-slaughter withdrawal period regardless of treatment duration.

STORAGE CONDITIONS

Store at controlled room temperature 20° to 25° C (68° to 77° F). Protect from light. Store syringes in carton or pail until used.

HOW SUPPLIED

SPECTRAMAST® LC Sterile Suspension is available in cartons containing 1 unbroken package of 12–10 mL PLASTET® Disposable Syringes and in pails containing 12 unbroken packages of 12-10 mL PLASTET® Disposable Syringes.

NO TITLE

Approved by FDA under NADA # 141-238
zoetis
Distributed by:
Zoetis Inc.
Kalamazoo, MI 49007
www.spectramast.com or call 1-888-963-8471
Revised: December 2022
40040154

PRINCIPAL DISPLAY PANEL - 12-10 mL Syringe Carton

40040155